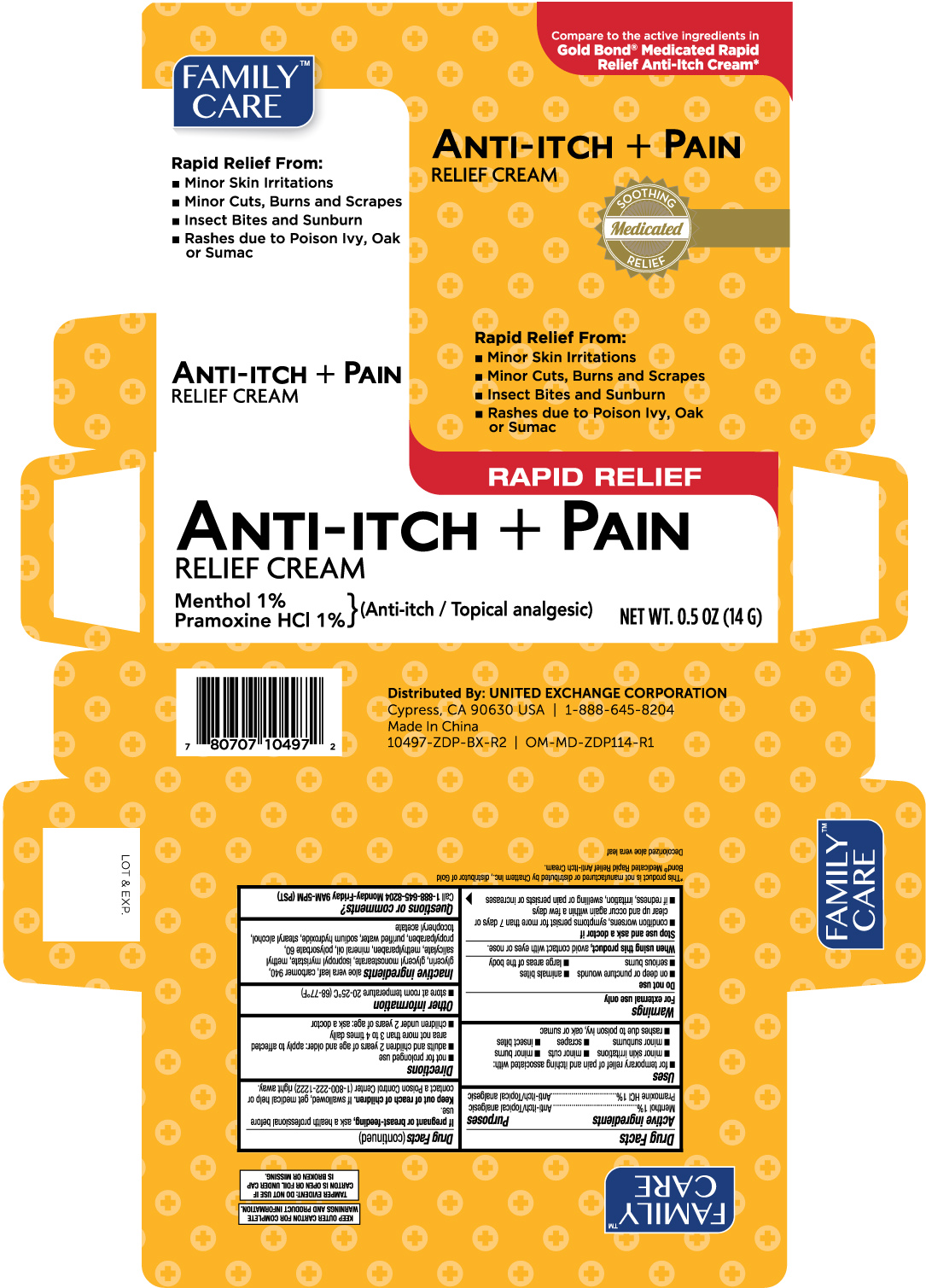 DRUG LABEL: Family Care Maximum Strength Medicated Anti Itch
NDC: 65923-104 | Form: CREAM
Manufacturer: United Exchange Corp.
Category: otc | Type: HUMAN OTC DRUG LABEL
Date: 20251021

ACTIVE INGREDIENTS: MENTHOL 10 mg/1 g; PRAMOXINE HYDROCHLORIDE 10 mg/1 g
INACTIVE INGREDIENTS: ALOE VERA LEAF; CARBOMER 940; GLYCERIN; GLYCERYL MONOSTEARATE; ISOPROPYL MYRISTATE; METHYLPARABEN; METHYL SALICYLATE; MINERAL OIL; POLYSORBATE 60; PROPYLPARABEN; STEARYL ALCOHOL; WATER; SODIUM HYDROXIDE; ALPHA-TOCOPHEROL ACETATE

Family Care Anti-Itch + Pain Relief Cream 0.5oz (10497)

Active Ingredients Purpose

Menthol 1%.........................................................................Anti-itch/Topical analgesic

Pramoxine HCl 1%..............................................................Anti-itch/Topical analgesic

Uses

- for temporary relief of pain and itching associated with:
- minor skin irritations
- minor cuts
- minor burns
- minor sunburns
- scrapes
- insect bites
- rashes due to poison ivy, oak, or sumac

Warnings For external use only.

Do not use

- on deep or puncture wounds
- animals bites
- serious burns
- large areas of the body

When using this product, avoid contact with eyes or nose.

Stop use and ask a doctor if

- condition worsens, symptoms persist for more than 7 days or clear up and occur again within a few days
- if redness, irritation, swelling or pain persists or increases

PREGNANCY OR BREAST FEEDING

If pregnant or breast-feeding, ask a health professional before use.

Keep out of reach of children. If swallowed, get medical help or contact a Poison control Center (1-800-222-1222) right away.

Directions

- not for prolonged use
- adults and children 2 years of age and older; apply to affected area not more than 3 to 4 times daily
- children under 2 years of age: ask a doctor.

Other information

- store at room temperature 20-25°C (68-77°F)

INACTIVE INGREDIENT

Inactive ingredients aloe vera leaf, carbomer 940, glycerin, glyceryl monostearate, isopropyl myristate, methyl salicylate, methylparaben, mineral oil, polysorbate 60, propylparaben, purified water, sodium hydroxide, stearyl alcohol, tocopheryl acetate

Questions or comments?

Call 1-888-645-8204 Monday-Friday 9AM-5PM (PST)

DOSAGE AND ADMINISTRATION

Distributed By: UNITED EXCHANGE CORPORATION

Cypress, CA 90630 USA | 1-888-645-8204

Made in China